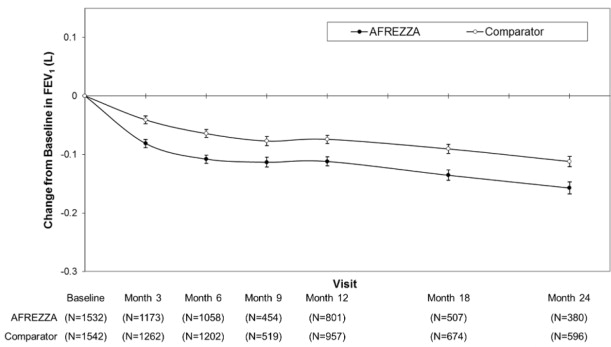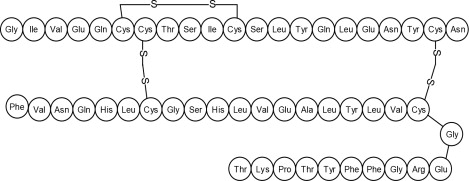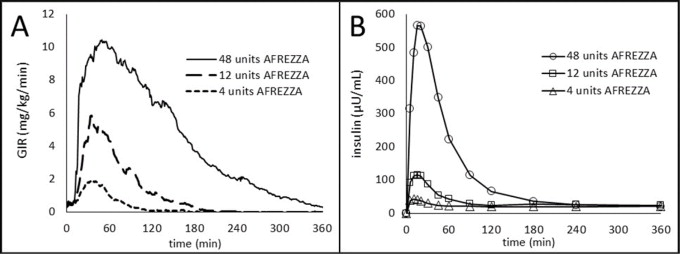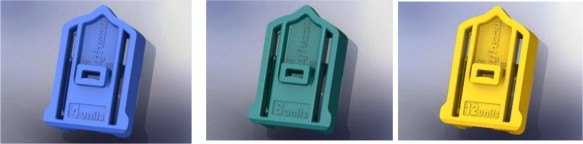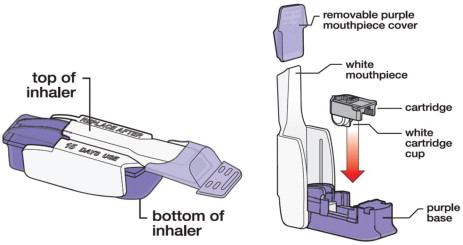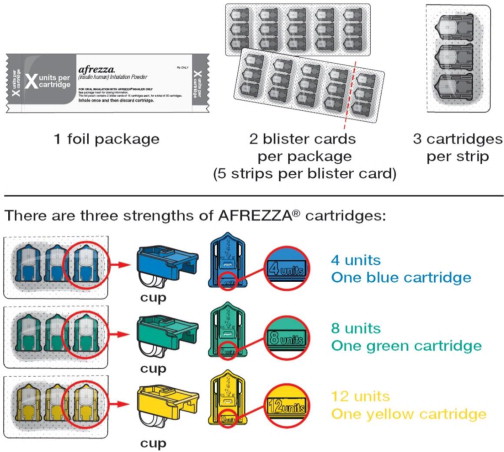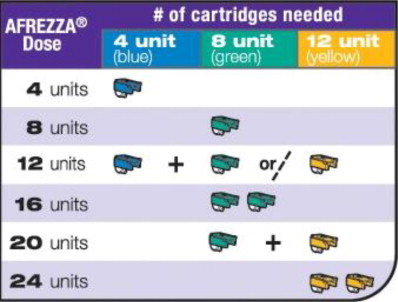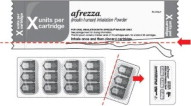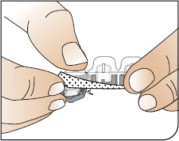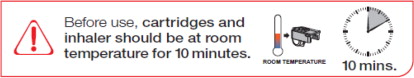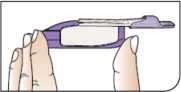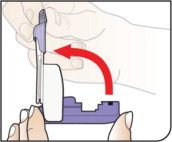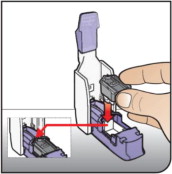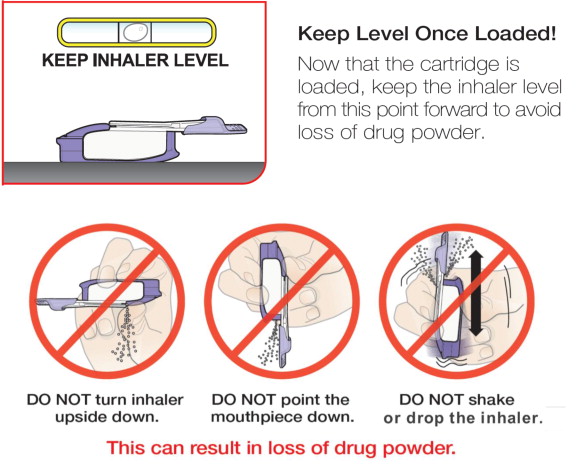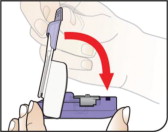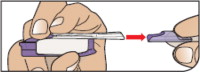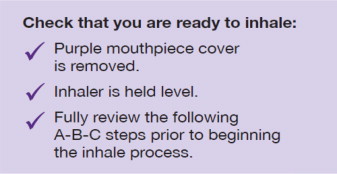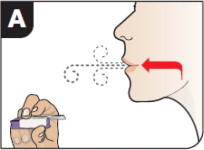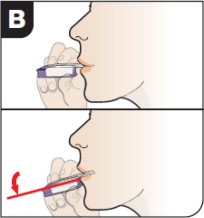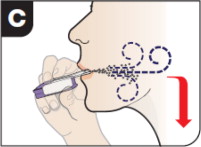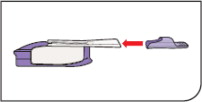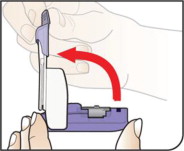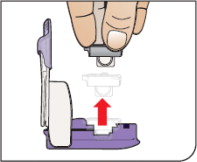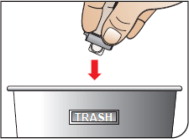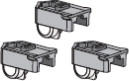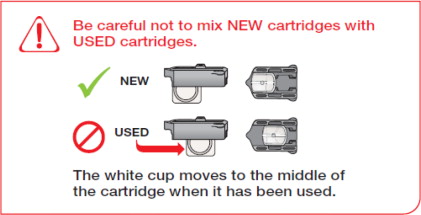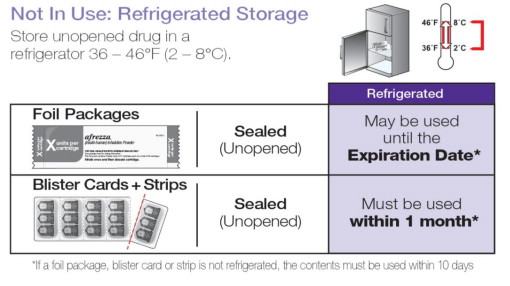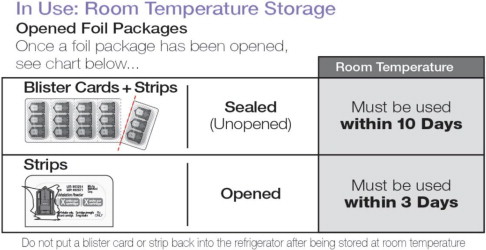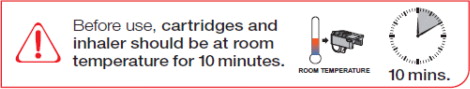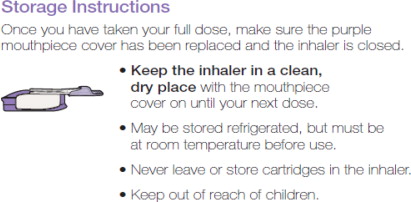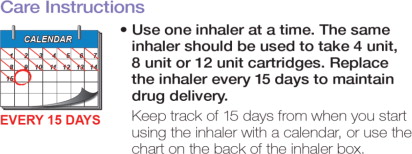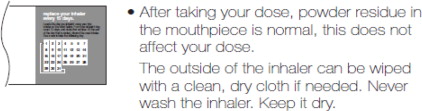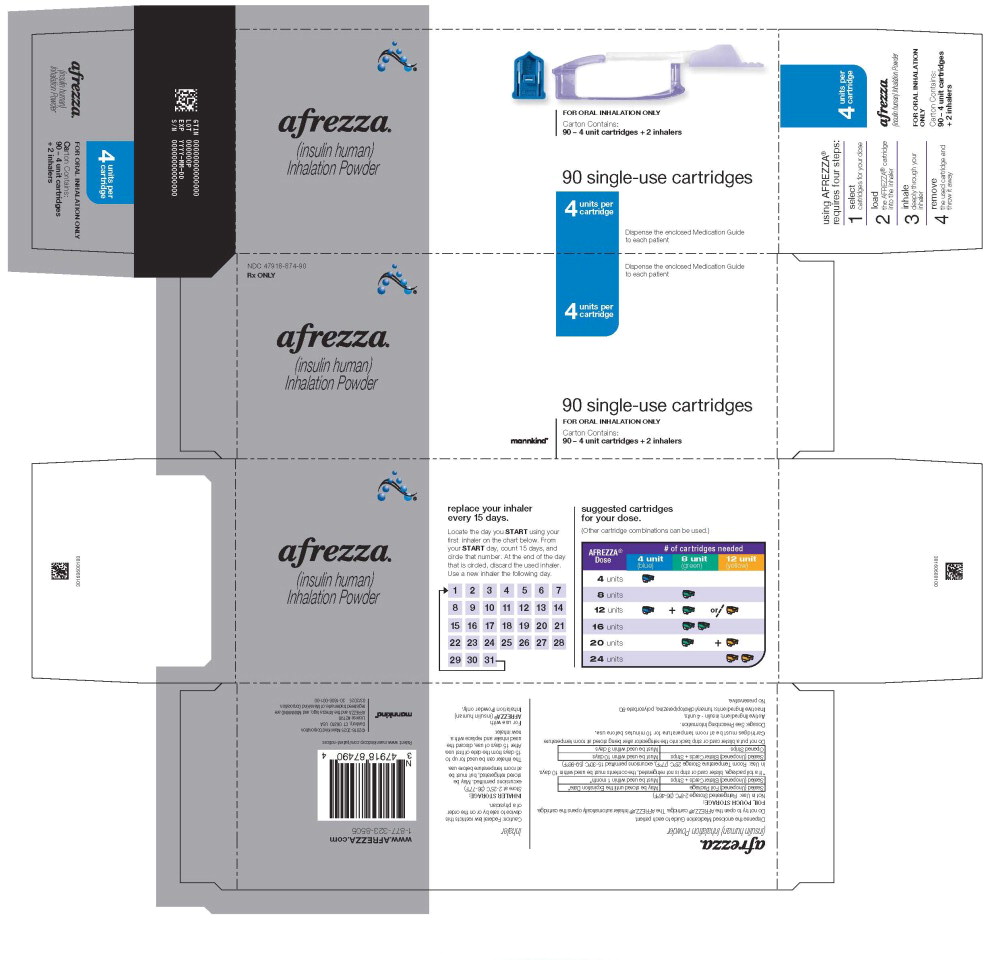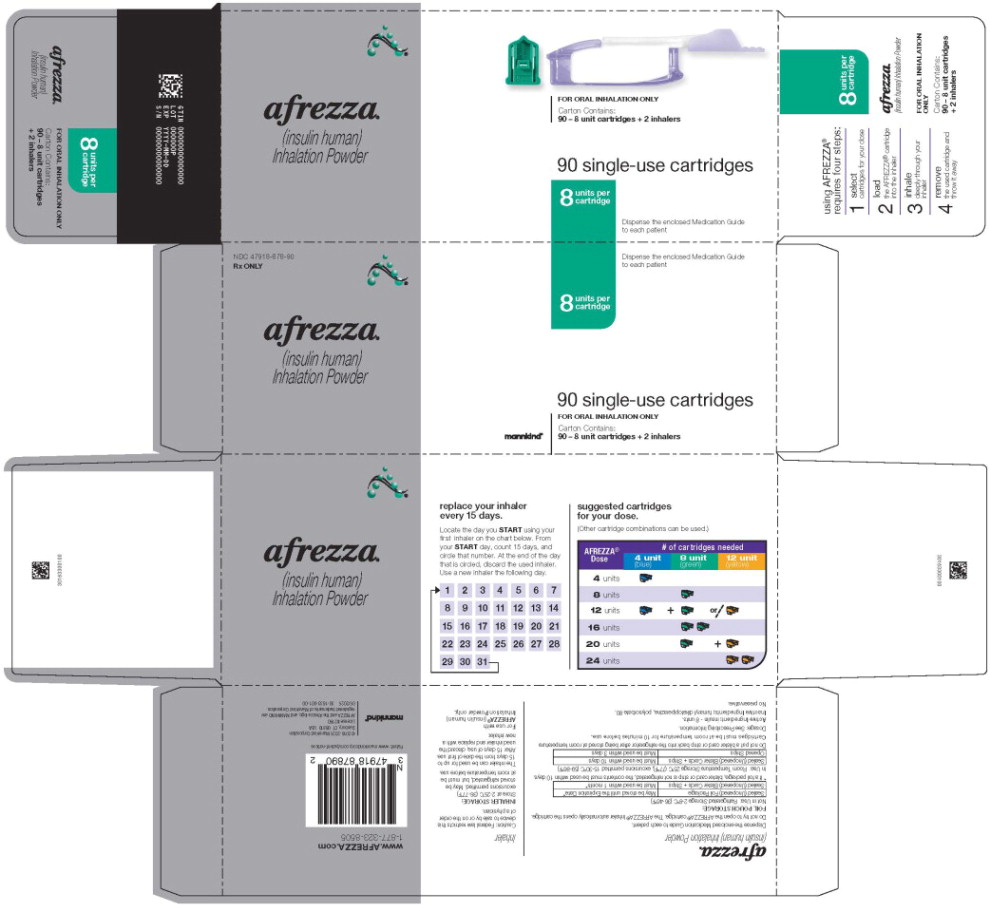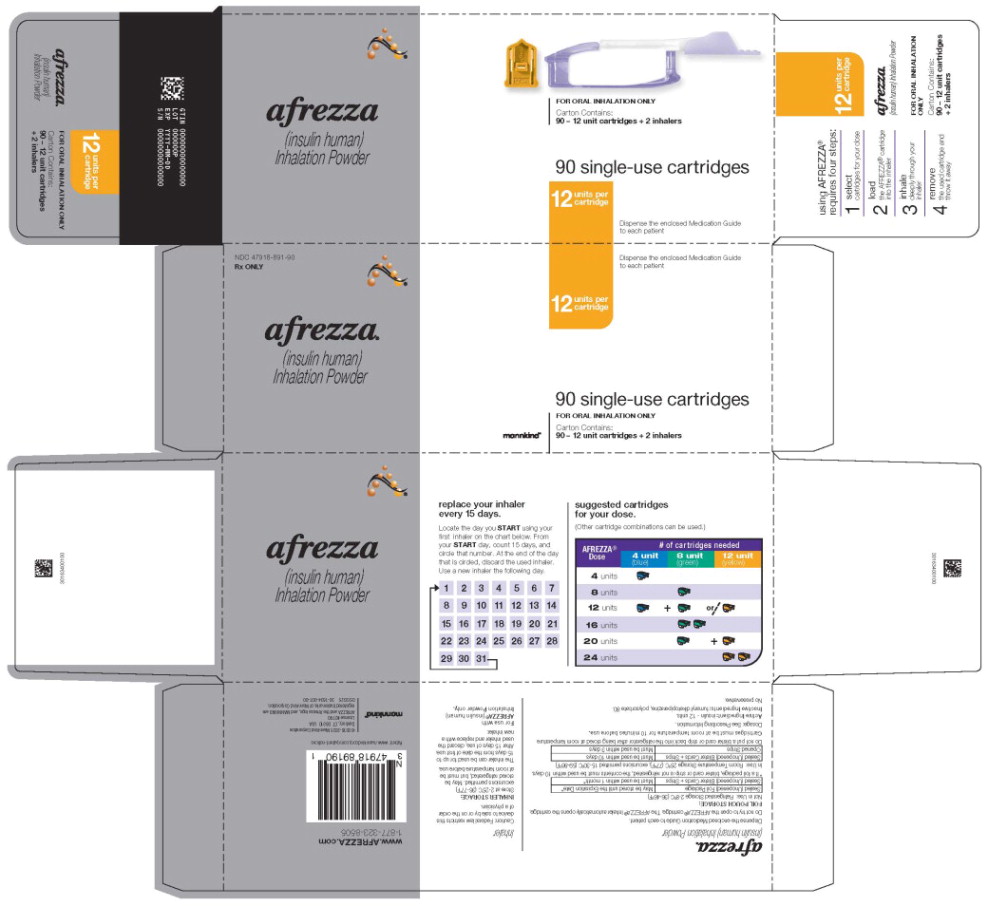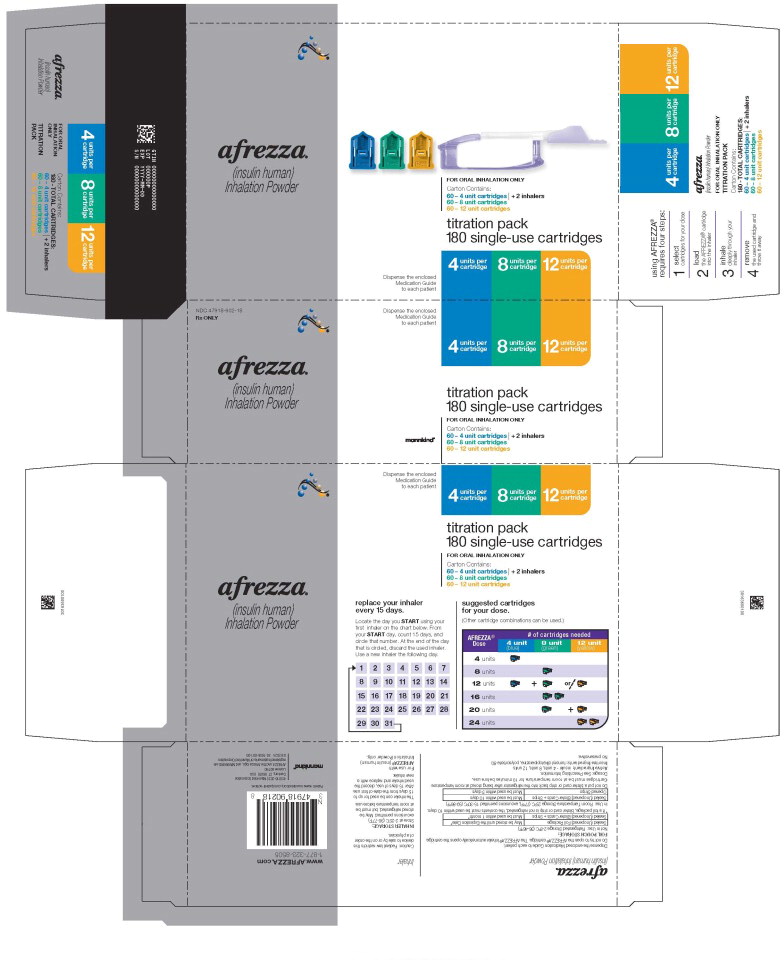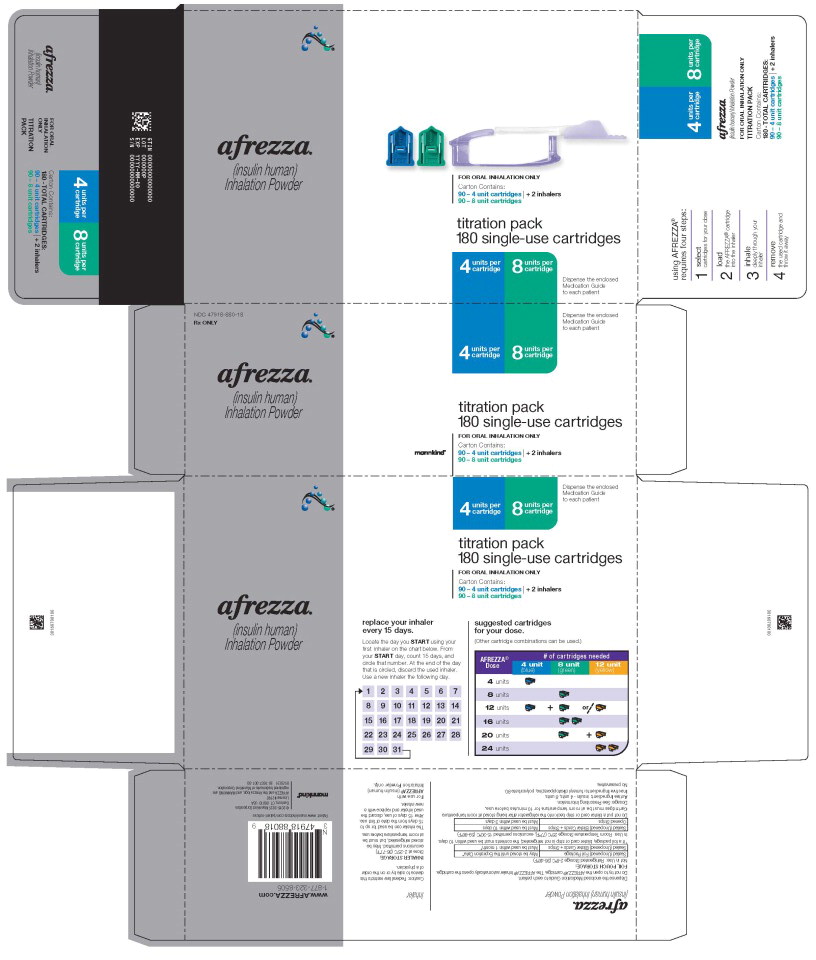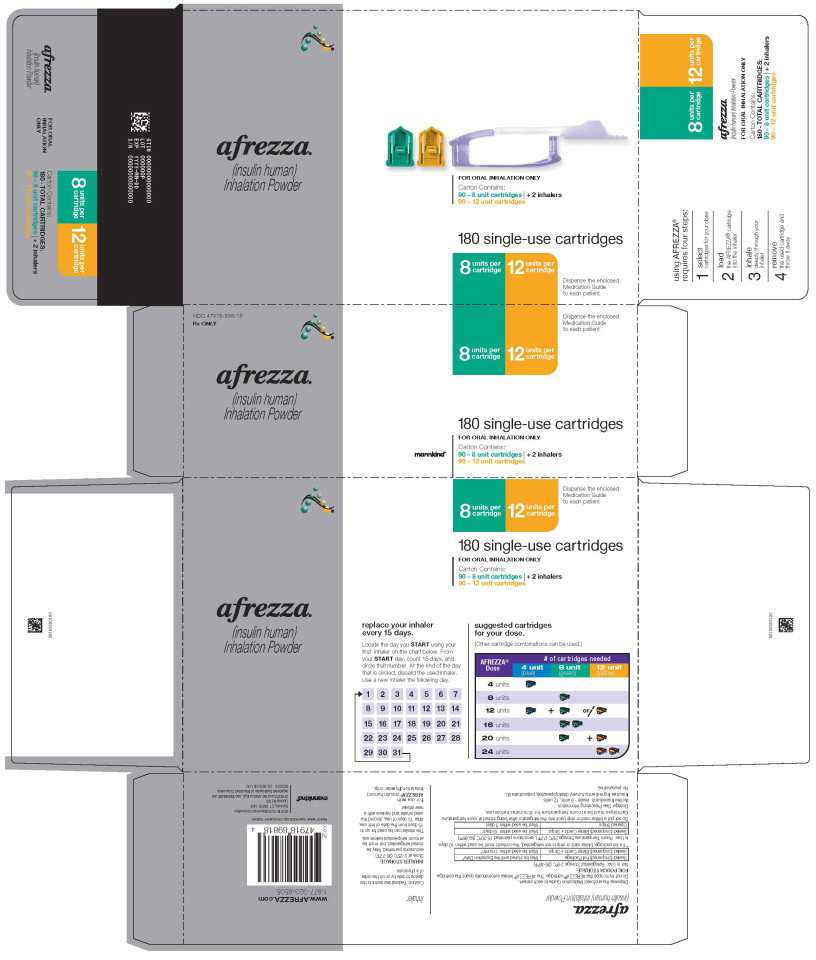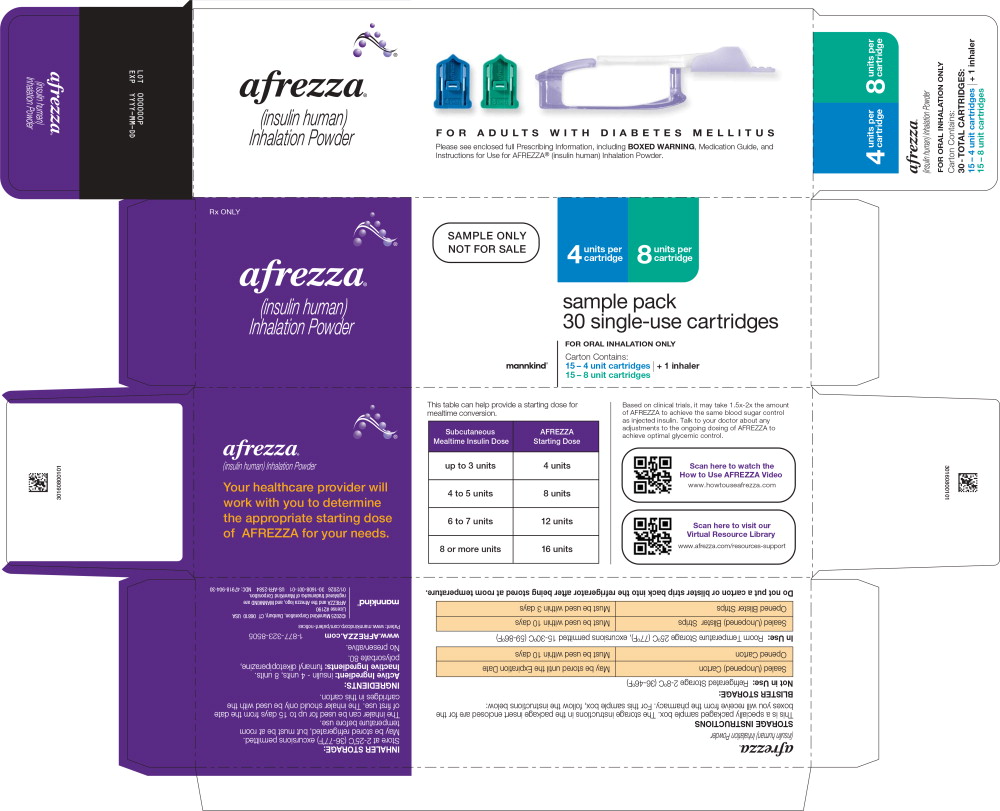 DRUG LABEL: AFREZZA

NDC: 47918-874 | Form: POWDER, METERED
Manufacturer: Mannkind Corporation
Category: prescription | Type: HUMAN PRESCRIPTION DRUG LABEL
Date: 20260203

ACTIVE INGREDIENTS: INSULIN HUMAN
 4 [arb'U]/1 1
INACTIVE INGREDIENTS: FUMARYL DIKETOPIPERAZINE; POLYSORBATE 80

HIGHLIGHTS OF PRESCRIBING INFORMATION

These highlights do not include all the information needed to use AFREZZA®safely and effectively. See full prescribing information for AFREZZA.
AFREZZA®(insulin human) inhalation powder, for oral inhalation use
Initial U.S. Approval: 2014

RECENT MAJOR CHANGES

Dosage and Administration, Recommended Starting Mealtime Dosage of AFREZZA (2.3) 1/2026

WARNING: RISK OF ACUTE BRONCHOSPASM IN PATIENTS WITH CHRONIC LUNG DISEASE

See full prescribing information for complete boxed warning.

- Acute bronchospasm has been observed in AFREZZA-treated patients with asthma and Chronic Obstructive Pulmonary Disease (COPD). (5.1)
- AFREZZA is contraindicated in patients with chronic lung disease such as asthma or COPD. (4)
- Before initiating AFREZZA, perform a detailed medical history, physical examination, and spirometry (FEV 1) to identify potential lung disease in all patients. (2.5), (5.1)

1 INDICATIONS AND USAGE

AFREZZA®is a rapid acting inhaled human insulin indicated to improve glycemic control in adult patients with diabetes mellitus. (1)

Limitations of Use:

- Not recommended for the treatment of diabetic ketoacidosis (DKA) (1)
- Not recommended in patients who smoke or who have recently stopped smoking (1)

2 DOSAGE AND ADMINISTRATION

- Only administer via oral inhalation using the AFREZZA inhaler (2.2)
- Administer at the beginning of each meal (2.2)
- See full prescribing information for the recommended starting mealtime dosage in insulin-naïve patients and patients who are using subcutaneous mealtime insulin, or pre-mixed insulin (2.3)
- Modify the mealtime AFREZZA dosage based on the patient's metabolic needs, blood glucose monitoring results, and glycemic control goal (2.4)
  If blood glucose control is not achieved with increased AFREZZA dosages, consider discontinuing AFREZZA (2.4)

3 DOSAGE FORMS AND STRENGTHS

Inhalation powder in single-use cartridges of: 4 units, 8 units, or 12 units (3)

4 CONTRAINDICATIONS

- During episodes of hypoglycemia (4)
- Chronic lung disease, such as asthma, or COPD (4)
- Hypersensitivity to any regular human insulin product or any of the inactive ingredients in AFREZZA (4)

5 WARNINGS AND PRECAUTIONS

- Hypoglycemia or Hyperglycemia with Changes in Insulin Regimen: Make necessary changes to a patient's insulin regimen under close medical supervision with increased frequency of blood glucose monitoring. For patients with type 2 diabetes mellitus, oral antidiabetic treatment dosage modifications may be needed. (5.2)
- Hypoglycemia(may be life-threatening): Increase frequency of glucose monitoring in patients at higher risk for hypoglycemia and those who have reduced symptomatic awareness of hypoglycemia. (5.3)
- Decline in Pulmonary Function: Assess pulmonary function (e.g., spirometry (FEV1)) at baseline, after 6 months of therapy, and annually, even in the absence of pulmonary symptoms. In patients who have a decline of ≥ 20% in FEV1from baseline, consider discontinuing AFREZZA. Consider more frequent monitoring of pulmonary function in patients with pulmonary symptoms (5.4)
- Lung Cancer: In patients with active lung cancer, a prior history of lung cancer, or in patients at risk for lung cancer, consider whether the benefits of AFREZZA use outweigh this potential risk. (5.5)
- Diabetic Ketoacidosis: In patients at risk for DKA, increase the frequency of glucose monitoring and consider changing to alternate route of insulin delivery. (5.6)
- Hypersensitivity Reactions: Severe, life-threatening, generalized allergy, including anaphylaxis, can occur with AFREZZA. If hypersensitivity reactions occur, discontinue AFREZZA, treat per standard of care and monitor until symptoms and signs resolve. (5.7)
- Hypokalemia(may be life-threatening): Monitor potassium levels in patients at risk of hypokalemia. (5.8)
- Fluid Retention and Heart Failure with Concomitant Use of PPAR-gamma Agonists:Observe for signs and symptoms of heart failure; consider dosage reduction or discontinuation if heart failure occurs. (5.9)

6 ADVERSE REACTIONS

The most common adverse reactions associated with AFREZZA (2% or greater incidence) are hypoglycemia, cough, and throat pain or irritation (6)

To report SUSPECTED ADVERSE REACTIONS, contact MannKind at 1-877-323-8505 or FDA at 1-800-FDA-1088 or www.fda.gov/medwatch.

7 DRUG INTERACTIONS

- Drugs that may increase the risk of hypoglycemia (7.1, 7.3)
- Drugs that may decrease blood glucose lowering effect of AFREZZA (7.2, 7.3)
- Drugs that may affect hypoglycemic signs and symptoms (7.4)

FULL PRESCRIBING INFORMATION

WARNING: RISK OF ACUTE BRONCHOSPASM IN PATIENTS WITH CHRONIC LUNG DISEASE

- Acute bronchospasm has been observed in AFREZZA-treated patients with asthma and Chronic Obstructive Pulmonary Disease (COPD) [see Warnings and Precautions (5.1)].
- AFREZZA is contraindicated in patients with chronic lung disease such as asthma or COPD [see Contraindications (4)].
- Before initiating AFREZZA, perform a detailed medical history, physical examination, and spirometry (FEV 1) to identify potential lung disease in all patients [see Dosage and Administration (2.5), Warnings and Precautions (5.1)].

1 INDICATIONS AND USAGE

AFREZZA®is indicated to improve glycemic control in adult patients with diabetes mellitus.

Limitations of Use:

- AFREZZA is not recommended for the treatment of diabetic ketoacidosis (DKA) [see Warning and Precautions (5.6)] .
- The safety and effectiveness of AFREZZA in patients who smoke have not been established. The use of AFREZZA is not recommended in patients who smoke or who have recently stopped smoking.

2 DOSAGE AND ADMINISTRATION

2.1 Lung Function Assessment Prior to Administration

AFREZZA is contraindicated in patients with chronic lung disease because of the risk of acute bronchospasm in these patients. Before initiating AFREZZA, perform a medical history, physical examination and spirometry (FEV1) in all patients to identify potential lung disease [see Contraindications (4) and Warnings and Precautions (5.1)].

2.2 Important Administration Information

Refer patients to the Instructions for Use for detailed instructions and visuals on how to prepare, administer, and store AFREZZA; use the AFREZZA cartridges; and use the AFREZZA inhaler.

- Only administer AFREZZA via oral inhalation using the AFREZZA Inhaler.
- Administer AFREZZA at the beginning of each meal.
- Administer AFREZZA using a single inhalation per cartridge (if the dose is greater than the contents of a single cartridge, more than one cartridge is needed) [see Dosage and Administration (2.3), Dosage Forms and Strengths (3)].
- To administer AFREZZA:
  - Keep the inhaler level with the white mouthpiece on top and purple base on the bottom after a cartridge has been inserted into the inhaler. Loss of drug effect can occur if the inhaler is turned upside down, held with the mouthpiece pointing down, shaken, or dropped after the cartridge has been inserted but before the dose has been administered. If any of the above occur, replace the cartridge before use.
  - Hold the inhaler away from the mouth and fully exhale.
  - After the inhaler is placed in the mouth and the lips form a seal, tilt the inhaler down towards the chin while keeping the head level.
  - With the mouth closed around the mouthpiece, inhale deeply through the inhaler.
  - Hold the breath for as long as comfortable and at the same time remove the inhaler from the mouth.
  - After holding the breath, exhale and continue to breathe normally.
- The AFREZZA Inhaler can be used for up to 15 days from the date of first use. After 15 days of use, discard the inhaler and replace it with a new inhaler.

2.3 Recommended Starting Mealtime Dosage of AFREZZA

Insulin naïve patients

The initial dosage of AFREZZA is 4 units inhaled at the beginning of each meal.

Switching from Other Mealtime (prandial) Insulin Regimens to AFREZZA

When switching from another insulin to AFREZZA, a different insulin dosage may be needed and increased frequency of blood glucose monitoring and monitoring for signs and symptoms of hypoglycemia may be needed [see Warnings and Precautions (5.2, 5.3), Clinical Pharmacology (12.2, 12.3)].

Subcutaneous, Mealtime (prandial) Insulin:

Follow the recommendations in Table 1to convert each injected mealtime insulin dosage (or bolus dosage for patients using insulin pumps) to the recommended mealtime dosage of AFREZZA.

Subcutaneous, Pre-Mixed Insulin:

- Refer to the prescribing information for the pre-mixed insulin to estimate the mealtime subcutaneous insulin dosage based on the product's pharmacokinetic and pharmacodynamic properties.
- Follow the recommendations in Table 1to convert each estimated injected mealtime dosage to an AFREZZA mealtime dose.
- If basal insulin is clinically indicated, refer to the prescribing information for the chosen basal insulin for dosage recommendations.

Table 1. Recommended Starting Mealtime Dosage of AFREZZA when Switching from Other Mealtime Insulin Regimens
Current Subcutaneous Mealtime Insulin Dosage | Starting Dosage of AFREZZA
Up to 3 units | 4 units
4 to 5 units | 8 units
6 to 7 units | 12 units
8 or more units | 16 units
* For AFREZZA doses exceeding the contents of a single cartridge at mealtime, use more than one cartridge. To achieve the required total mealtime dosage, use a combination of 4 unit, 8 unit, and 12 unit cartridges. When titrating dosages above 16 units after the initial conversion dosage, use combinations of different cartridges [see Dosage and Administration (2.4), Dosage Forms and Strengths (3), How Supplied/Storage and Handling (16)] .

2.4 Mealtime AFREZZA Dosage Modification

- Modify the mealtime AFREZZA dosage based on the patient's metabolic needs, blood glucose monitoring results, and glycemic control goal.
- Dosage modifications may be needed with changes in physical activity, changes in meal patterns (i.e., macronutrient content or timing of food intake), changes in renal or hepatic function or during acute illness [see Warnings and Precautions (5.3) and Use in Specific Populations (8.6, 8.7)].
- Increase the frequency of blood glucose monitoring during titration of AFREZZA. If blood glucose control is not achieved with increased AFREZZA dosages, consider discontinuing AFREZZA.

2.5 Dosage Modifications for Drug Interactions

Dosage modification may be needed when:

- AFREZZA is used concomitantly with certain drugs that increase and/or decrease the glucose lowering effect [see Drug Interactions (7.1, 7.2, 7.3)].
- Switching from another insulin to AFREZZA [see Dosage and Administration (2.3) and Warnings and Precautions (5.2)]

3 DOSAGE FORMS AND STRENGTHS

Inhalation Powder: single-use cartridges containing 4 units, 8 units or 12 units of insulin human as white powder.

4 CONTRAINDICATIONS

AFREZZA is contraindicated:

- During episodes of hypoglycemia [see Warnings and Precautions (5.3)].
- In patients with chronic lung disease, such as asthma or COPD, because of the risk of acute bronchospasm [see Warnings and Precautions (5.1)].
- In patients with a previous severe hypersensitivity reaction to any regular human insulin product or any of the inactive ingredients in AFREZZA. Severe, life-threatening, generalized allergy, including anaphylaxis, can occur with AFREZZA [see Warnings and Precautions (5.7)].

5 WARNINGS AND PRECAUTIONS

5.1 Acute Bronchospasm in Patients with Chronic Lung Disease

Because of the risk of acute bronchospasm, AFREZZA is contraindicated in patients with chronic lung disease such as asthma or COPD [see Contraindications (4)] . Before initiating therapy with AFREZZA, evaluate patients with a medical history, physical examination, and spirometry (FEV1) to identify potential underlying lung disease.

Acute bronchospasm has been observed in AFREZZA-treated patients with asthma and COPD. In a study of patients with asthma whose bronchodilators were temporarily withheld for assessment, bronchoconstriction and wheezing following AFREZZA dosing was reported in 29% (5/17) and 0% (0/13) of patients with and without a diagnosis of asthma, respectively. In this study, a mean decline in FEV1of 400 mL was observed 15 minutes after a single AFREZZA dose in patients with asthma. In a subset study of 8 patients with COPD, a mean decline in FEV1of 200 mL was observed 18 minutes after a single AFREZZA dose.

5.2 Hypoglycemia or Hyperglycemia with Changes in Insulin Regimen

Changes in an insulin regimen (e.g., insulin strength, manufacturer, injection site or type, or method of administration) may affect glycemic control and predispose to hypoglycemia [see Warnings and Precautions (5.3)] or hyperglycemia. If clinically indicated, make any necessary changes to a patient's insulin regimen under close medical supervision with increased frequency of blood glucose monitoring. For patients with type 2 diabetes, dosage modifications of concomitant oral antidiabetic treatment may be needed [see Drug Interactions (7.1, 7.2, and 7.3)] .

5.3 Hypoglycemia

Hypoglycemia is the most common adverse reaction associated with insulins, including AFREZZA. Severe hypoglycemia can cause seizures, may be life-threatening, or cause death. Hypoglycemia can impair concentration ability and reaction time; this may place an individual and others at risk in situations where these abilities are important (e.g., driving or operating other machinery).

AFREZZA's time action profile impacts the timing of hypoglycemia following inhalation of the drug product [see Clinical Pharmacology (12.3)] . Hypoglycemia can occur suddenly, and symptoms may differ across patients and change over time in the same patient. Symptomatic awareness of hypoglycemia may be less pronounced in patients with longstanding diabetes, in patients with diabetic nerve disease, in patients using medications that block the sympathetic nervous system (e.g., beta-blockers) [see Drug Interactions (7)], or in patients who experience recurrent hypoglycemia.

Risk Factors and Mitigation Strategies for Hypoglycemia

The risk of hypoglycemia after use of AFREZZA is related to the duration of action of the insulin and, in general, is highest when the glucose lowering effect of the insulin is maximal [See Clinical Pharmacology (12.3)] . The glucose lowering effect time course of AFREZZA may vary in different individuals or at different times in the same individual and depends on many conditions [see Clinical Pharmacology (12.2)] . Other factors which may increase the risk of hypoglycemia include changes in meal pattern (e.g., macronutrient content or timing of meals), changes in level of physical activity, or changes to concomitantly administered medication [see Drug Interactions (7)]. Patients with renal or hepatic impairment may be at higher risk of hypoglycemia [see Use in Specific Populations (8.6, 8.7)]. Advise patients to recognize and manage hypoglycemia and self-monitor glucose. In patients at higher risk for hypoglycemia and patients who have reduced symptomatic awareness of hypoglycemia, increased frequency of glucose monitoring is recommended.

5.4 Decline in Pulmonary Function

AFREZZA causes a decline in pulmonary function over time as measured by FEV1. In clinical trials excluding patients with chronic lung disease and lasting up to 2 years, AFREZZA-treated patients experienced a small [40 mL (95% CI: -80, -1)] but greater FEV1decline than comparator-treated patients. The FEV1decline was noted within the first 3 months, and persisted for the entire duration of therapy (up to 2 years of observation). In this population, the annual rate of FEV1decline did not appear to worsen with increased duration of use. The effects of AFREZZA on pulmonary function for treatment duration longer than 2 years has not been established. There are insufficient data in long term studies to draw conclusions regarding reversal of the effect on FEV1after discontinuation of AFREZZA. The observed changes in FEV1were similar in patients with type 1 and type 2 diabetes.

Assess pulmonary function (e.g., spirometry) at baseline, after the first 6 months of therapy, and annually thereafter, even in the absence of pulmonary symptoms. In patients who have a decline of ≥ 20% in FEV1from baseline, consider discontinuing AFREZZA. Consider more frequent monitoring of pulmonary function in patients with pulmonary symptoms such as wheezing, bronchospasm, breathing difficulties, or persistent or recurring cough. If symptoms persist, discontinue AFREZZA [see Adverse Reactions (6)] .

5.5 Lung Cancer

In clinical trials, two cases of lung cancer, one in controlled trials and one in uncontrolled trials (2 cases in 2,750 patient-years of exposure), were observed in patients exposed to AFREZZA while no cases of lung cancer were observed in patients exposed to comparators (0 cases in 2,169 patient-years of exposure). In both cases, a prior history of heavy tobacco use was identified as a risk factor for lung cancer. Two additional cases of lung cancer (squamous cell and lung blastoma) occurred in non-smokers exposed to AFREZZA and were reported by investigators after clinical trial completion. These data are insufficient to determine whether AFREZZA has an effect on lung or respiratory tract tumors.

In patients with active lung cancer, a prior history of lung cancer, or in patients at risk for lung cancer, consider whether the benefits of AFREZZA use outweigh this potential risk.

5.6 Diabetic Ketoacidosis

In clinical trials enrolling patients with type 1 diabetes, DKA was more common in AFREZZA-treated patients (0.43%; n=13) than in comparator-treated patients (0.14%; n=3). Patients with type 1 diabetes should always use AFREZZA concomitantly with basal insulin. In patients at risk for DKA, such as those with an acute illness or infection, increase the frequency of glucose monitoring and consider discontinuing AFREZZA and giving insulin using an alternate route of administration.

5.7 Hypersensitivity Reactions

Severe, life-threatening, generalized allergy, including anaphylaxis, can occur with AFREZZA.

If hypersensitivity reactions occur, discontinue AFREZZA, treat per standard of care and monitor until symptoms and signs resolve [see Adverse Reactions (6)] . AFREZZA is contraindicated in patients with a previous severe hypersensitivity reaction to any regular human insulin product or any of the inactive ingredients in AFREZZA [see Contraindications (4)] .

5.8 Hypokalemia

All insulin products, including AFREZZA, cause a shift in potassium from the extracellular to intracellular space, possibly leading to hypokalemia. Untreated hypokalemia may cause respiratory paralysis, ventricular arrhythmia, and death.

Monitor potassium levels in AFREZZA-treated patients at risk for hypokalemia (e.g., patients using potassium-lowering medications, patients taking medications sensitive to serum potassium concentrations and patients receiving intravenously administered insulin).

5.9 Fluid Retention and Heart Failure with Concomitant Use of PPAR-gamma Agonists

Thiazolidinediones (TZDs), which are peroxisome proliferator-activated receptor (PPAR)-gamma agonists, can cause dose-related fluid retention, particularly when used in combination with insulin. Fluid retention may lead to or exacerbate heart failure.

Patients treated with insulin, including AFREZZA, and a PPAR-gamma agonist should be observed for signs and symptoms of heart failure. If heart failure develops, it should be managed according to current standards of care, and discontinuation or dose reduction of the PPAR-gamma agonist should be considered.

6 ADVERSE REACTIONS

The following serious adverse reactions are described below and elsewhere in the labeling:

- Acute bronchospasm in patients with chronic lung disease [see Warnings and Precautions (5.1)]
- Hypoglycemia [see Warnings and Precautions (5.3)]
- Decline in pulmonary function [see Warnings and Precautions (5.4)]
- Lung cancer [see Warnings and Precautions (5.5)]
- Diabetic ketoacidosis [see Warnings and Precautions (5.6)]
- Hypersensitivity reactions [see Warnings and Precautions (5.7)]

6.1 Clinical Trials Experience

Because clinical trials are conducted under widely varying conditions, adverse reaction rates observed in the clinical trials of a drug cannot be directly compared to rates in the clinical trials of another drug and may not reflect the rates observed in practice.

The data described below reflect exposure of 3,017 patients to AFREZZA and include 1,026 patients with type 1 diabetes and 1,991 patients with type 2 diabetes. The mean exposure duration was 8.2 months for patients with type 1 diabetes and those with type 2 diabetes. In the overall population:

- 1,874 patients were exposed to AFREZZA for 6 months and 724 patients for greater than one year.
- 620 and 1,254 patients with type 1 and type 2 diabetes, respectively, were exposed to AFREZZA for up to 6 months.
- 238 and 486 patients with type 1 and type 2 diabetes, respectively, were exposed to AFREZZA for greater than one year (median exposure was 1.8 years).

AFREZZA was studied in placebo and active-controlled trials (n = 3 and n = 10, respectively).

The mean age of the population was 50 years and 20 patients were older than 75 years of age; 51% of the population were males; 83% were White, 5% were Black or African American, and 2% were Asian; 10% were Hispanic. At baseline, the type 1 diabetes population had diabetes for an average of 17 years and had a mean HbA1c of 8.3%, and the type 2 diabetes population had diabetes for an average of 11 years and had a mean HbA1c of 8.8%. At baseline, 33% of the population reported peripheral neuropathy, 32% reported retinopathy and 20% had a history of cardiovascular disease.

Table 2shows the frequency of common adverse reactions, excluding hypoglycemia, associated with the use of AFREZZA in the pool of controlled trials in type 2 diabetes patients that occurred more commonly on AFREZZA than on placebo and/or comparator and occurred in at least 2% of patients treated with AFREZZA.

Table 2. Common Adverse Reactions That Occurred in ≥ 2% in Patients with Type 2 Diabetes Mellitus (excluding Hypoglycemia) Treated with AFREZZA
 | AFREZZA (n = 1,991) % | Placebo* (n = 290) % | Non-placebo comparators (n=1,363) %
Cough | 26 4 3 3 2 2 2 | 20 4 3 1 1 1 0.3 | 5 1 2 2 1 1 1
Throat pain or irritation | 26 4 3 3 2 2 2 | 20 4 3 1 1 1 0.3 | 5 1 2 2 1 1 1
Headache | 26 4 3 3 2 2 2 | 20 4 3 1 1 1 0.3 | 5 1 2 2 1 1 1
Diarrhea | 26 4 3 3 2 2 2 | 20 4 3 1 1 1 0.3 | 5 1 2 2 1 1 1
Productive cough | 26 4 3 3 2 2 2 | 20 4 3 1 1 1 0.3 | 5 1 2 2 1 1 1
Fatigue | 26 4 3 3 2 2 2 | 20 4 3 1 1 1 0.3 | 5 1 2 2 1 1 1
Nausea | 26 4 3 3 2 2 2 | 20 4 3 1 1 1 0.3 | 5 1 2 2 1 1 1
*Carrier particle without insulin was used as placebo [see Description (11.1)] .

Table 3shows the frequency of common adverse reactions, excluding hypoglycemia, associated with the use of AFREZZA in the pool of active-controlled trials in type 1 diabetes patients. These adverse reactions were not present at baseline, occurred more commonly on AFREZZA than on comparator, and occurred in at least 2% of patients treated with AFREZZA.

Table 3. Common Adverse Reactions That Occurred in ≥ 2% in Patients with Type 1 Diabetes Mellitus (excluding Hypoglycemia) Treated with AFREZZA
 | AFREZZA (n=1,026) | Subcutaneous Insulin (n = 835)
Cough | 29 | 5
Throat pain or irritation | 6 | 2
Headache | 5 | 3
Pulmonary function test decreased | 3 | 1
Bronchitis | 3 | 2
Urinary tract infection | 2 | 2

Hypoglycemia

Hypoglycemia is the most commonly observed adverse reaction in patients using insulin, including AFREZZA [see Warnings and Precautions (5.3)] . The incidence of severe and non-severe hypoglycemia in AFREZZA-treated patients versus placebo-treated patients with type 2 diabetes is shown in Table 4. A hypoglycemic episode was recorded if a patient reported symptoms of hypoglycemia with or without a blood glucose value consistent with hypoglycemia. Severe hypoglycemia was defined as an event with symptoms consistent with hypoglycemia requiring the assistance of another person and associated with either a blood glucose value consistent with hypoglycemia or prompt recovery after treatment for hypoglycemia.

Table 4. Incidence of Severe and Non-Severe Hypoglycemia in a Placebo-Controlled Study of Patients with Type 2 Diabetes
 | AFREZZA (N=177) | Placebo (N=176)
Severe Hypoglycemia | 5% | 2%
Non-Severe Hypoglycemia | 67% | 30%

Cough

Approximately 27% of patients treated with AFREZZA reported cough, compared to approximately 5% of patients treated with comparator. In clinical trials, cough was the most common reason for discontinuation of AFREZZA therapy (3% of AFREZZA-treated patients).

Pulmonary Function Decline

In clinical trials lasting up to 2 years, excluding patients with chronic lung disease, patients treated with AFREZZA had a 40 mL (95% CI: -80, -1) greater decline from baseline in forced expiratory volume in one second (FEV1) compared to patients treated with comparator anti-diabetes treatments. The decline occurred during the first 3 months of therapy and persisted over 2 years (Figure 1). A decline in FEV1of ≥ 15% occurred in 6% of AFREZZA-treated patients compared to 3% of comparator-treated patients [see Warnings and Precautions (5.4)].

Figure 1. Mean (+/-SE) Change in FEV 1 (Liters) from Baseline for Type 1 and Type 2 Diabetes Patients

Weight Gain

Weight gain has occurred with some insulin therapies, including AFREZZA. Weight gain has been attributed to the anabolic effects of insulin and the decrease in glycosuria. In a clinical trial of patients with type 2 diabetes [see Clinical Studies (14.3)] , there was a mean 0.49 kg weight gain among AFREZZA-treated patients compared with a mean 1.13 kg weight loss among placebo-treated patients.

6.2 Postmarketing Experience

The following adverse reaction has been identified during post approval use of AFREZZA. Because these reactions are reported voluntarily from a population of uncertain size, it is not always possible to reliably estimate their frequency or establish a causal relationship to drug exposure: bronchospasm.

7 DRUG INTERACTIONS

7.1 Drugs That May Increase the Risk of Hypoglycemia

The risk of hypoglycemia associated with AFREZZA use may be increased with antidiabetic agents, ACE inhibitors, angiotensin II receptor blocking agents, disopyramide, fibrates, fluoxetine, monoamine oxidase inhibitors, pentoxifylline, pramlintide, salicylates, somatostatin analogs (e.g., octreotide), and sulfonamide antibiotics. Dose modification and increased frequency of glucose monitoring may be required when AFREZZA is given concomitantly with these drugs.

7.2 Drugs That May Decrease the Blood Glucose Lowering Effect of AFREZZA

The glucose lowering effect of AFREZZA may be decreased when given concomitantly with atypical antipsychotics (e.g., olanzapine and clozapine), corticosteroids, danazol, diuretics, estrogens, glucagon, isoniazid, niacin, oral contraceptives, phenothiazines, progestogens (e.g., in oral contraceptives), protease inhibitors, somatropin, sympathomimetic agents (e.g., albuterol, epinephrine, terbutaline) and thyroid hormones. Dosage modification and increased frequency of glucose monitoring may be required when AFREZZA is given concomitantly with these drugs.

7.3 Drugs That May Increase or Decrease the Blood Glucose Lowering Effect of AFREZZA

The glucose lowering effect of AFREZZA may be increased or decreased when used concomitantly with alcohol, beta-blockers, clonidine, and lithium salts. Pentamidine may cause hypoglycemia, which may sometimes be followed by hyperglycemia. Dosage modification and increased frequency of glucose monitoring may be required when AFREZZA is given concomitantly with these drugs.

7.4 Drugs That May Affect Hypoglycemia Signs and Symptoms

The signs and symptoms of hypoglycemia may be blunted when beta-blockers, clonidine, guanethidine, and reserpine are given concomitantly with AFREZZA.

8 USE IN SPECIFIC POPULATIONS

8.1 Pregnancy

Risk Summary

Limited available data with AFREZZA use in pregnant women are insufficient to determine drug-associated risks for adverse developmental outcomes. Available information from published studies with human insulin use during pregnancy has not reported a clear association with human insulin and adverse developmental outcomes (see Data). There are risks to the mother and fetus associated with poorly controlled diabetes in pregnancy (see Clinical Considerations). In animal reproduction studies, there were no adverse developmental outcomes with subcutaneous administration of carrier particles (vehicle without insulin) to pregnant rats during organogenesis at doses 21 times the human daily dose of 99 mg AFREZZA, based on AUC (see Data) .

The estimated background risk of major birth defects is 6-10% in women with pre-gestational diabetes with HbA1c >7 and has been reported to be as high as 20-25% in women with HbA1c >10. The estimated background risk of miscarriage for the indicated population is unknown. In the U.S. general population, the estimated background risk of major birth defects and miscarriage in clinically recognized pregnancies is 2-4% and 15-20%, respectively.

Clinical Considerations

Disease-associated maternal and/or embryo/fetal risk

Poorly controlled diabetes in pregnancy increases the maternal risk for DKA, pre-eclampsia, spontaneous abortions, preterm delivery, stillbirth, and delivery complications. Poorly controlled diabetes increases the fetal risk for major birth defects, stillbirth, and macrosomia- related morbidity.

Data

Human Data

There are limited data with AFREZZA use in pregnant women. Published data do not report a clear association with human insulin and major birth defects, miscarriage, or adverse maternal or fetal outcomes when human insulin is used during pregnancy. However, these studies cannot definitely establish the absence of any risk because of methodological limitations including small sample size and lack of blinding.

Animal Data

In pregnant rats given subcutaneous doses of 10, 30, and 100 mg/kg/day of carrier particles (vehicle without insulin) from gestation day 6 through 17 (organogenesis), no major malformations were observed at doses up to 100 mg/kg/day (21 times the human systemic exposure at a daily dose of 99 mg AFREZZA, based on AUC).

In pregnant rabbits given subcutaneous doses of 2, 10, and 100 mg/kg/day of carrier particles (vehicle without insulin) from gestation day 7 through 19 (organogenesis), adverse maternal effects were observed in all dose groups (at human systemic exposure following a daily dose of 99 mg AFREZZA, based on AUC).

In pregnant rats given subcutaneous doses of 10, 30, and 100 mg/kg/day of carrier particles (vehicle without insulin) from gestation day 7 through lactation day 20 (weaning), decreased epididymis and testes weights were observed in F1 male offspring, however, no decrease in fertility was noted, and impaired learning were observed in F1 pups at ³ 30 mg/kg/day (6 times the human systemic exposure at a daily dose of 99 mg AFREZZA, based on AUC).

8.2 Lactation

Risk Summary

There are no data on the presence of AFREZZA in human milk, the effects on the breastfed infant, or the effects on milk production. One small published study reported that exogenous subcutaneous insulin was present in human milk. No adverse effects in infants were noted. The carrier particles are present in rat milk (see Data). Potential adverse reactions that are related to inhalational administration of AFREZZA are unlikely to be associated with potential exposure of AFREZZA through breast milk. The developmental and health benefits of breastfeeding should be considered along with the mother's clinical need for AFREZZA and any potential adverse effects on the breastfed infant from AFREZZA or from the underlying maternal condition.

Data

Subcutaneous administration of the carrier particle in lactating rats resulted in excretion of the carrier particle in rat milk at levels that were approximately 10% of the maternal exposure. Given the results of the rat study, it is highly likely that the insulin and carrier in AFREZZA are excreted in human milk.

8.4 Pediatric Use

The safety and effectiveness of AFREZZA to improve glycemic control in pediatric patients with diabetes mellitus have not been established.

8.5 Geriatric Use

In the AFREZZA clinical studies ,671 (12%) patients were 65 years of age or older, of which 42 (0.8%) were 75 years of age or older. In these studies, 381 (13%) of AFREZZA-treated patients were 65 years of age or older, of which 20 (0.7%) were 75 years of age or older. No overall differences in effectiveness of AFREZZA have been observed between patients 65 years of age and older and younger adult patients [see Clinical Studies (14)] . Clinical studies of AFREZZA did not include sufficient numbers of patients 65 years of age and older to determine whether there were differences in safety between these patients and younger adult patients.

Pharmacokinetic and pharmacodynamic studies to assess the effect of age on pharmacokinetics or pharmacodynamics on insulin human, respectively, have not been conducted.

8.6 Hepatic Impairment

The effect of hepatic impairment on the pharmacokinetics of AFREZZA has not been studied. Frequent glucose monitoring and a lower dosage may be necessary in AFREZZA-treated patients with hepatic impairment [see Warnings and Precautions (5.3)] .

8.7 Renal Impairment

The effect of renal impairment on the pharmacokinetics of AFREZZA has not been studied. Some studies with human insulin have shown increased circulating levels of insulin in patients with renal failure. Frequent glucose monitoring and a lower dosage may be necessary in AFREZZA-treated patients with renal impairment [see Warnings and Precautions (5.3)] .

10 OVERDOSAGE

Excess insulin administration may cause hypoglycemia and hypokalemia [see Warnings and Precautions (5.3, 5.8)] .

Mild episodes of hypoglycemia due to insulin overdose can usually be treated with oral glucose. Adjustments in drug dosage, meal patterns, or exercise, may be needed.

Severe episodes of hypoglycemia (due to insulin overdose) with coma, seizure, or neurologic impairment may be treated with intramuscular or subcutaneous glucagon or concentrated intravenous glucose. After apparent clinical recovery from hypoglycemia, continued observation and additional carbohydrate intake may be necessary to avoid recurrence of hypoglycemia. Hypokalemia should be corrected appropriately.

In the event of an overdose of AFREZZA, consider contacting the Poison Help line (1-800-222-1222) or a medical toxicologist for additional overdosage management recommendation

11 DESCRIPTION

11.1 AFREZZA Cartridges

Human insulin is a rapid acting human insulin produced by recombinant DNA technology utilizing a non-pathogenic laboratory strain of Escherichia coli(K12). Chemically, human insulin has the empirical formula C257H383N65O77S6and a molecular weight of 5808. Human insulin has the following primary amino acid sequence:

AFREZZA (human insulin) inhalation powder is available in single-use plastic cartridges filled with a white powder containing insulin (human), which is administered via oral inhalation using the AFREZZA Inhaler only.

Insulin is adsorbed onto carrier particles consisting of fumaryl diketopiperazine (FDKP) and polysorbate 80.

AFREZZA Inhalation Powder is a dry powder supplied as 4 unit, 8 unit or 12 unit cartridges.

11.2 AFREZZA Inhaler

The AFREZZA Inhaler is breath-powered by the patient. When the patient inhales through the device, the powder is aerosolized and delivered to the lung. The amount of AFREZZA delivered to the lung will depend on individual patient factors.

12 CLINICAL PHARMACOLOGY

12.1 Mechanism of Action

Insulin lowers blood glucose levels in adult patients with diabetes mellitus by stimulating peripheral glucose uptake by skeletal muscle and fat, and by inhibiting hepatic glucose production. Insulin inhibits lipolysis in adipocytes, inhibits proteolysis, and enhances protein synthesis.

12.2 Pharmacodynamics

The time course of insulin action (i.e., glucose lowering) may vary considerably in different patients or within the same patient, or when switching from subcutaneous mealtime insulin to AFREZZA. The average pharmacodynamic profile [i.e., glucose lowering effect measured by glucose infusion rate (GIR) over time in a euglycemic clamp study] after administration of a single AFREZZA dose of 4, 12, and 48 units in 30 patients with type 1 diabetes is shown in Figure 2(A), and key characteristics regarding the timing of the effects are described in Table 5:

Table 5. Timing of Insulin Effect (i.e., mean pharmacodynamics effect) After Administration of a Single AFREZZA Dose in Patients (N=30) with Type 1 Diabetes Mellitus
Parameter for Insulin Effect | AFREZZA 4 units | AFREZZA 12 units | AFREZZA 48 units
Time to first measurable effect | ~12 minutes | ~12 minutes | ~12 minutes
Time to peak effect | ~35 minutes | ~45 minutes | ~55 minutes
Time for effect to return to baseline | ~90 minutes | ~180 minutes | ~270 minutes

Figure 2. Results After Administration of AFREZZA 4, 12, and 48 Units in Patients with T1DM (N=30)

A) Mean Insulin Effect (Baseline-Corrected Glucose Infusion Rate); and

B) Pharmacokinetic (Baseline-Corrected Serum Insulin Concentration Profiles)

On average, the pharmacodynamics effect of AFREZZA, measured as area under the glucose infusion rate – time curve (AUC GIR) increased linearly with doses up to 48 units (106, 387, and 1581 mg/kg for 4, 12, and 48 units doses, respectively).

Intrapatient variability in AUC GIR and GIRmaxwas approximately 28% (95% CI 21-42%) and 27% (95% CI 20-40%), respectively.

12.3 Pharmacokinetics

The area under the plasma concentration versus time curve (AUC) of insulin increased dose proportionally up to 48 units. Intrapatient variability of AUC and peak concentration (Cmax) of insulin was approximately 16% (95% CI 12-23%) and 21% (95% CI 16-30%), respectively.

Absorption

The pharmacokinetic profiles for orally inhaled AFREZZA 4, 12, and 48 units from a study in 30 patients with type 1 diabetes are shown in Figure 2(B). A higher maximum plasma insulin concentration was achieved at an earlier timepoint in this study when patients were switched from subcutaneous mealtime insulin to AFREZZA [see Dosage and Administration (2.3)]. The time to maximum serum insulin concentration (tmax) ranged from 10-20 minutes after oral inhalation of 4 to 48 units of AFREZZA.

Elimination

The apparent terminal half-life ranged from 120 to 206 minutes. Serum insulin concentrations declined to baseline by approximately 60 to 240 minutes.

Metabolism and Excretion

The metabolism and excretion of AFREZZA are comparable to regular human insulin.

Carrier Particles

Clinical pharmacology studies showed that carrier particles [see Description (11.1)] are not metabolized and are eliminated unchanged in the urine following the lung absorption. Following oral inhalation of AFREZZA, a mean of 39% of the inhaled dose of carrier particles was distributed to the lungs and a mean of 7% of the dose was swallowed. The swallowed fraction was not absorbed from the GI tract and was eliminated unchanged in the feces.

Drug Interaction Studies

Bronchodilators and Inhaled Steroids

Albuterol increased the AUC insulin after AFREZZA administration by 25% in patients with asthma [see Drug Interactions (7.2)]. AFREZZA is contraindicated in patients with asthma.

In a study in healthy volunteers no significant change in insulin exposure was observed when fluticasone was administered following AFREZZA administration.

12.6 Immunogenicity

The observed incidence of anti-drug antibodies is highly dependent on the sensitivity and specificity of the assay. Differences in assay methods preclude meaningful comparisons of the incidence of anti-drug antibodies in the studies described below with the incidence of anti-drug antibodies in other studies, including those of insulin human or of other insulin human products.

Increases in anti-insulin antibody concentrations were observed in patients treated with AFREZZA. Increases in anti-insulin antibodies were observed more frequently in patients treated with AFREZZA than in patients treated with subcutaneously injected mealtime insulin. There was no clinically significant effect of anti-drug antibodies on safety or effectiveness (as measured by HbA1c and fasting plasma glucose) of AFREZZA over the treatment duration of the studies which spanned 3 to 24 months.

13 NONCLINICAL TOXICOLOGY

13.1 Carcinogenesis

In a 104 week carcinogenicity study, rats were given doses up to 46 mg/kg/day of the carrier and up to 1.23 mg/kg/day of insulin, by nose-only inhalation. No increased incidence of tumors was observed at systemic exposures equivalent to the insulin at a daily AFREZZA dose of 99 mg, based on a comparison of relative body surface areas across species.

13.2 Mutagenesis

No increased incidence of tumors was observed in a 26 week carcinogenicity study in transgenic mice (Tg-ras-H2) given doses up to 75 mg/kg/day of carrier and up to 5 mg/kg/day of AFREZZA.

AFREZZA was not genotoxic in Ames bacterial mutagenicity assay and in the chromosome aberration assay, using human peripheral lymphocytes with or without metabolic activation. The carrier alone was not genotoxic in the in vivo mouse micronucleus assay.

13.3 Impairment of Fertility

In fertility study in male and female rats at subcutaneous doses of 10, 30, and 100 mg/kg/day of carrier (vehicle without insulin), there were no adverse effects on male fertility at doses up to 100 mg/kg/day. In female rats dosed 2 weeks prior to mating until gestation day 7, there was increased pre- and post-implantation loss at 100 mg/kg/day but not at 30 mg/kg/day (21 times and 6 times, respectively the human systemic exposure at a daily dose of 99 mg AFREZZA, based on AUC).

14 CLINICAL STUDIES

14.1 Overview of Clinical Studies of AFREZZA in Adults for Diabetes Mellitus

AFREZZA has been studied in adults with type 1 diabetes in combination with basal insulin. The efficacy of AFREZZA, in combination with basal insulin, in type 1 diabetes patients was compared to insulin aspart in combination with basal insulin.

AFREZZA has been studied in adults with type 2 diabetes in combination with oral antidiabetic drugs. The efficacy of AFREZZA in type 2 diabetes patients was compared to placebo inhalation.

14.2 Adults with Type 1 Diabetes

Patients with inadequately controlled type 1 diabetes participated in a 24-week, open-label, active-controlled study to evaluate the glucose lowering effect of mealtime AFREZZA used in combination with a basal insulin. Following a 4-week basal insulin optimization period, 344 patients were randomized to AFREZZA by oral inhalation (n=174) or insulin aspart given subcutaneously (n=170) at each meal of the day. All patients received basal insulin. Mealtime insulin doses were titrated to glycemic goals for the first 12 weeks and kept stable for the last 12 weeks of the study.

Results

At Week 24, treatment with mealtime AFREZZA and basal insulin provided a mean reduction in HbA1c that met the pre-specified non-inferiority margin of 0.4%. AFREZZA and basal insulin provided less HbA1c reduction than insulin aspart and basal insulin, and the difference was statistically significant. More patients in the insulin aspart and basal insulin group achieved the HbA1c target of ≤7% (Table 6).

Table 6. Results at Week 24 in an Active-Controlled Study of Mealtime AFREZZA plus Basal Insulin in Adults with Type 1 Diabetes
Efficacy Parameter | AFREZZA + Basal Insulin (N=174) | Insulin Aspart + Basal Insulin (N=170)
HbA1c (%)
Baseline (adjusted meana) | 7.94 | 7.92
Change from baseline (adjusted meana,b) | -0.21 | -0.40
Difference from insulin aspart (adjusted meana,b) (95% CI) | 0.19 (0.02, 0.36)
Percentage of patients achieving HbA1c ≤ 7%c | 14% | 27%
Fasting Plasma Glucose (mg/dL)
Baseline (adjusted meana) | 153.9 | 151.6
Change from baseline (adjusted meana, b) | -25.3 | 10.2
Difference from insulin aspart (adjusted meana, b) (95% CI) | -35.4 (-56.3, -14.6)
aAdjusted mean was obtained using a Mixed Model Repeated Measures (MMRM) approach with HbA1c or FPG as the dependent variable and treatment, visit, region, basal insulin stratum, and treatment by visit interaction as fixed factors, and corresponding baseline as a covariate. An autoregression (1) [AR(1)] covariance structure was used.
bData at 24 weeks were available from 131 (75%) and 150 (88%) patients randomized to the AFREZZA and insulin aspart groups, respectively.
cThe percentage was calculated based on the number of patients randomized to the trial.

14.3 Adults with Type 2 Diabetes

A total of 479 adult patients with type 2 diabetes inadequately controlled on optimal/maximally tolerated doses of metformin only, or 2 or more oral antidiabetic (OAD) agents participated in a 24-week, double-blind, placebo-controlled study. Following a 6-week run-in period, 353 patients were randomized to AFREZZA by oral inhalation (n=177) or an inhaled placebo powder without insulin (n=176). Insulin doses were titrated for the first 12 weeks and kept stable for the last 12 weeks of the study. OADs doses were kept stable in the study.

Results

At Week 24, treatment with AFREZZA plus OADs provided a mean reduction in HbA1c that was statistically significantly greater compared to the HbA1c reduction observed in the placebo plus OADs group (Table 7).

Table 7. Results at Week 24 in a Placebo-Controlled Study of AFREZZA in Adults with Type 2 Diabetes Inadequately Controlled on Oral Antidiabetic Agents
Efficacy Parameter | AFREZZA + Oral Anti-Diabetic Agents (N=177) | Placebo + Oral Anti-Diabetic Agents (N=176)
HbA1c (%)
Baseline (adjusted meana) | 8.25 | 8.27
Change from baseline (adjusted meana,b) | -0.82 | -0.42
Difference from placebo (adjusted meana,b) (95% CI) | -0.40 (-0.57, -0.23)
Percentage (%) of patients achieving HbA1C ≤7%c | 32% | 15%
Fasting Plasma Glucose (mg/dL)
Baseline (adjusted meana) | 175.9 | 175.2
Change from baseline (adjusted meana,b) | -11.2 | -3.8
Difference from placebo (adjusted meana,b) (95% CI) | -7.4 (-18.0, 3.2)
aAdjusted mean was obtained using a Mixed Model Repeated Measures (MMRM) approach with HbA1c or FPG as the dependent variable and treatment, visit, region, and treatment by visit interaction as fixed factors, and corresponding baseline as a covariate. An autoregression (1) [AR(1)] covariance structure was used.
bData at 24 weeks without rescue therapy were available from 139 (79%) and 129 (73%) patients randomized to the AFREZZA and placebo groups, respectively.
cThe percentage was calculated based on the number of patients randomized to the trial.

16 HOW SUPPLIED/STORAGE AND HANDLING

AFREZZA (insulin human) Inhalation Powder is available as 4 unit, 8 unit and 12 unit single-use cartridges. Three cartridges are contained in a single cavity of a blister strip. Each card contains 5 blister strips (each containing three cartridges) separated by perforations for a total of 15 cartridges. Two cards of the same cartridge strength are packaged in a foil laminate overwrap (30 cartridges per foil package).

The cartridges are color-coded, blue for 4 units, green for 8 units and yellow for 12 units. Each cartridge is marked with “afrezza” and “4 units”, “8 units” or “12 units”.

The AFREZZA Inhaler is individually packaged in a clear overwrap. The inhaler is fully assembled with a removable mouthpiece cover. The AFREZZA Inhaler can be used for up to 15 days from the date of first use. After 15 days of use, the inhaler must be discarded and replaced with a new inhaler.

AFREZZA (insulin human) Inhalation Powder is available in the following configurations:

NDC | Cartridge Strength | Quantity of Cartridges per Strength | Total Quantity of Cartridges per Kit | Total Units in Kit | Number of Inhalers
47918-874-90 | 4 units | 90 | 90 | 360 Units | 2
47918-878-90 | 8 units | 90 | 90 | 720 Units | 2
47918-891-90 | 12 units | 90 | 90 | 1,080 Units | 2
47918-898-18 | 8 units, 12 units | 90 | 180 | 1,800 Units | 2
47918-880-18 (Titration Pack) | 4 units, 8 units | 90 | 180 | 1,080 Units | 2
47918-902-18 (Titration Pack) | 4 units, 8 units, 12 units | 60 | 180 | 1,440 Units | 2

Storage:

Not in Use: Refrigerated Storage 2ºC to 8ºC (36ºF to 46ºF)

Sealed (Unopened) Foil Package | May be stored until the Expiration Date*
Sealed (Unopened) Blister Cards and Strips | Must be used within 1 month*
* If a foil package, blister card or strip is not refrigerated, the contents must be used within 10 days.

In Use: Room Temperature Storage 25ºC (77ºF), excursions permitted 15ºC to 30ºC (59ºF to 86ºF)

Sealed (Unopened) Blister Cards and Strips | Must be used within 10 days
Opened Strips | Must be used within 3 days

Do not put a blister card or strip back into the refrigerator after being stored at room temperature.

Inhaler Storage:

Store refrigerated or at room temperature 2ºC to 25ºC (36ºF to 77ºF); excursions permitted. Inhaler may be stored refrigerated, but should be at room temperature before use.

Handling:

Before use, cartridges should be at room temperature for 10 minutes.

17 PATIENT COUNSELING INFORMATION

Advise the patient to read the FDA-approved patient labeling (Medication Guideand Instructions for Use).

Instruct patients to use AFREZZA only with the AFREZZA inhaler.

Acute Bronchospasm in Patients with Chronic Lung Disease

Advise patients that if they experience any respiratory difficulty after inhalation of AFREZZA, they should report it to their healthcare provider immediately for assessment [see Warnings and Precautions (5.1)] .

Hypoglycemia

Instruct patients on self-management procedures including glucose monitoring, proper inhalation technique, and management of hypoglycemia and hyperglycemia, especially at initiation of AFREZZA therapy. Instruct patients on handling of special situations such as intercurrent conditions (illness, stress, or emotional disturbances), an inadequate or skipped insulin dose, inadvertent administration of an increased insulin dose, inadequate food intake, or skipped meals [see Warnings and Precautions (5.3)] .

Inform patients that their ability to concentrate and react may be impaired as a result of hypoglycemia. Advise patients who have frequent hypoglycemia or reduced or absent warning signs of hypoglycemia to use caution when driving or operating machinery.

Advise patients that changes in insulin regimen can predispose to hyperglycemia or hypoglycemia and that changes in insulin regimen should be made under close medical supervision [see Warnings and Precautions (5.2)].

Decline in Pulmonary Function

Inform patients that AFREZZA can cause a decline in lung function [see Warnings and Precautions (5.4)].

Lung Cancer

Inform patients to promptly report any signs or symptoms potentially related to lung cancer [see Warnings and Precautions (5.5)].

Diabetic Ketoacidosis

Instruct patients to carefully monitor their blood glucose during illness, infection, and other risk situations for DKA and to contact their healthcare provider if their blood glucose control worsens [see Warnings and Precautions (5.6)].

Hypersensitivity Reactions

Advise patients that hypersensitivity reactions can occur with insulin therapy including AFREZZA. Inform patients on the symptoms of hypersensitivity reactions [see Warnings and Precautions (5.7)].

Manufactured by: MannKind Corporation, Danbury, CT 06810
US License No. #2190
© 2016 – 2024 MannKind Corporation

AFREZZA is a registered trademark of MannKind Corporation
Patent: www.mannkindcorp.com/patent-notices

MEDICATION GUIDE
AFREZZA® (uh-FREZZ-uh)
(insulin human)
inhalation powder, for oral inhalation use

What is the most important information I should know about AFREZZA?
AFREZZA can cause serious side effects, including:

- Sudden lung problems (bronchospasms). Do not use AFREZZA if you have long-term (chronic) lung problems such as asthma or chronic obstructive pulmonary disease (COPD).Before starting AFREZZA, your healthcare provider will give you a breathing test to check how your lungs are working.

What is AFREZZA?

- AFREZZA is a man-made insulin that is breathed-in through your lungs (inhaled) and is used to control high blood sugar in adults with diabetes mellitus.
- AFREZZA is not for use to treat diabetic ketoacidosis. AFREZZA must be used with basal insulin in people who have type 1 diabetes mellitus.
- It is not known if AFREZZA is safe and effective for use in people who smoke. AFREZZA is not for use in people who smoke or have recently stopped smoking (less than 6 months).
- It is not known if AFREZZA is safe and effective in children under 18 years of age.

Who should not use AFREZZA?
Do not use AFREZZA if you:

- Have chronic lung problems such as asthma or COPD.
- Are allergic to regular human insulin or any of the ingredients in AFREZZA. See the end of this Medication Guide for a complete list of ingredients in AFREZZA.
- Are having an episode of low blood sugar (hypoglycemia).

What should I tell my healthcare provider before using AFREZZA?
Before using AFREZZA, tell your healthcare provider about all your medical conditions, including if you:

- Have lung problems such as asthma or COPD
- Have or have had lung cancer
- Are using any inhaled medications
- Smoke or have recently stopped smoking
- Have kidney or liver problems
- Are pregnant, planning to become pregnant, or are breastfeeding. AFREZZA may harm your unborn or breastfeeding baby.

Tell your healthcare provider about all the medicines you take, including prescription and over-the-counter medicines, vitamins or herbal supplements.
Before you start using AFREZZA, talk to your healthcare provider about low blood sugar and how to manage it.

How should I use AFREZZA?

- Read the detailed Instructions for Usethat comes with your AFREZZA.
- Take AFREZZA exactly as your healthcare provider tells you to. Your healthcare provider should tell you how much AFREZZA to use and when to use it.
- Know the strength of AFREZZA you use. Do notchange the amount of AFREZZA you use unless your healthcare provider tells you to.
- Take AFREZZA at the beginning of your meal.
- Check your blood sugar levels.Ask your healthcare provider what your blood sugar should be and when you should check your blood sugar levels.
- Keep AFREZZA and all medicines out of the reach of children.

Your dose of AFREZZA may need to change because of:

- Change in level of physical activity or exercise, weight gain or loss, increased stress, illness, change in diet, or because of other medicines you take.

What should I avoid while using AFREZZA?
While using AFREZZA do not:

- Drive or operate heavy machinery, until you know how AFREZZA affects you
- Drink alcohol or use over-the-counter medicines that contain alcohol
- Smoke

What are the possible side effects of AFREZZA?

- AFREZZA may cause serious side effects that can lead to death, including:

See “ What is the most important information I should know about AFREZZA?”

- Low blood sugar (hypoglycemia).Signs and symptoms that may indicate low blood sugar include:
  - Dizziness or light-headedness, sweating, confusion, headache, blurred vision, slurred speech, shakiness, fast heartbeat, anxiety, irritability or mood change, hunger.
- Decreased lung function.Your healthcare provider should check how your lungs are working before you start using AFREZZA, 6 months after you start using it and yearly after that.
- Lung cancer.In studies of AFREZZA in people with diabetes, lung cancer occurred in a few more people who were taking AFREZZA than in people who were taking other diabetes medications. There were too few cases to know if lung cancer was related to AFREZZA. If you have lung cancer, you and your healthcare provider should decide if you should use AFREZZA.
- Diabetic ketoacidosis.Talk to your healthcare provider if you have an illness. Your AFREZZA dose or how often you check your blood sugar may need to be changed.
- Severe allergic reaction (whole body reaction). Get medical help right away if you have any of these signs or symptoms of a severe allergic reaction:
  - A rash over your whole body, trouble breathing, a fast heartbeat, or sweating.
- Low potassium in your blood (hypokalemia).
- Heart failure.Taking certain diabetes pills called thiazolidinediones or “TZDs” with AFREZZA may cause heart failure in some people. This can happen even if you have never had heart failure or heart problems before. If you already have heart failure it may get worse while you take TZDs with AFREZZA. Your healthcare provider should monitor you closely while you are taking TZDs with AFREZZA. Tell your healthcare provider if you have any new or worse symptoms of heart failure including:
  - Shortness of breath, swelling of your ankles or feet, sudden weight gain.
  Treatment with TZDs and AFREZZA may need to be changed or stopped by your healthcare provider if you have new or worse heart failure.

Get emergency medical help if you have:

- Trouble breathing, shortness of breath, fast heartbeat, swelling of your face, tongue, or throat, sweating, extreme drowsiness, dizziness, confusion.

The most common side effects of AFREZZA include:

- Low blood sugar (hypoglycemia), cough, sore throat.

These are not all the possible side effects of AFREZZA.Call your doctor for medical advice about side effects. You may report side effects to FDA at 1-800-FDA-1088 (1-800-332-1088).

General information about the safe and effective use of AFREZZA.
Medicines are sometimes prescribed for purposes other than those listed in a Medication Guide. Do not use AFREZZA for a condition for which it was not prescribed. Do not give AFREZZA to other people, even if they have the same symptoms that you have. It may harm them.
This Medication Guide summarizes the most important information about AFREZZA. If you would like more information, talk with your healthcare provider. You can ask your pharmacist or healthcare provider for information about AFREZZA that is written for health professionals.

What are the ingredients in AFREZZA?
Active ingredient:human insulin
Inactive ingredients:fumaryl diketopiperazine, polysorbate 80

AFREZZA is a registered trademark of MannKind Corporation
Patent: www.mannkindcorp.com/patent-notices
Manufactured by: MannKind Corporation, Danbury, CT 06810
US License No. #2190
© 2016 – 2023 MannKind Corporation
For more information, go to www.AFREZZA.com or call MannKind Corporation at 1-877-323-8505.

This Medication Guide has been approved by the U.S. Food and Drug Administration

Revised 02/2023

INSTRUCTIONS FOR USE

AFREZZA® (uh-FREZZ-uh)

(insulin human)

inhalation powder, for oral inhalation use

This “Instructions for Use” contains information on how to use AFREZZA®(insulin human) Inhalation Powder.

Read this Instructions for Use before you start using AFREZZA and each time you get a new AFREZZA Inhaler. There may be new information. This information does not take the place of talking to your healthcare provider about your medical condition or your treatment.

Your healthcare provider should show you how to use your AFREZZA Inhaler the right way before you use it for the first time.

Important information about AFREZZA:

- AFREZZA starts acting fast,so take your medicine right before you eat a meal.
- AFREZZA comes in 3 strengths(see Figure A):
  - 4 units (blue cartridge)
  - 8 units (green cartridge)
  - 12 units (yellow cartridge)

- If your prescribed AFREZZA dose is higher than 12 units, you will need to use more than 1 cartridge.
- If you need to use more than 1 cartridge for your dose, throw away the used cartridge before getting a new one. You can tell when a cartridge has been used, because the cup has moved to the center.
- Do not try to open the AFREZZA cartridges.The AFREZZA Inhaler opens the cartridge automatically during use.
- AFREZZA cartridges should only be used with the AFREZZA Inhaler. Do nottry to breathe in the AFREZZA insulin powder in any other way. Do notput cartridges in your mouth and do notswallow cartridges.
- Use only 1 AFREZZA Inhaler at a time. The same inhaler should be used for the 4 unit, 8 unit or 12 unit cartridges.
- Store the inhaler in a clean, dry place with the mouthpiece cover on until your next dose.
- Throw away your AFREZZA Inhaler after 15 days and get a new one.

If you are having problems with your AFREZZA Inhaler or if it breaks and you need a new one, call 1-877-323-8505.

Know your AFREZZA Inhaler:

Know your AFREZZA cartridges:

How to take your dose of AFREZZA:
Always be sure you have the right number of AFREZZA cartridges for your dose available before you start. AFREZZA cartridges must only be used with the AFREZZA Inhaler.

Step 1: Select the AFREZZA cartridges for your dose

Use the figure below(Figure B) to select the AFREZZA cartridges for your dose.
Note: If your prescribed AFREZZA dose is higher than 12 units,you will need to use more than 1 cartridge. If you have any questions about which cartridges you should use to administer your prescribed AFREZZA dose, talk with your prescribing health care provider.

Open Packages
Remove a blister card from the foil package.
Tear along perforation to remove one strip.

Push Cartridges to Remove
Remove a cartridge from the strip by pressing on the clear side to push the cartridge out. Remove the right number of cartridges for your dose. Pushing on the cup will not damage the cartridge.
AFREZZA cartridges left over in an opened strip must be used within 3 days.

Before Proceeding:
Check that you have the right AFREZZA cartridge(s) for your dose.
Use only 1 inhaler for multiple cartridges. Throw away your AFREZZA Inhaler after 15 days and get a new one.

Step 2: Loading a cartridge

Hold Inhaler
Hold the inhaler level in one (1) hand with the white mouthpiece on the top and purple base on the bottom.

Open Inhaler
Open the inhaler by lifting the white mouthpiece to a vertical position.
Before you put the AFREZZA cartridge in your inhaler, make sure it has been at room temperature for 10 minutes.

Place Cartridge
Hold the cartridge with the cup facing down.
Line up the cartridge with the opening in the inhaler. The pointed end of the cartridge should line up with the pointed end in the inhaler.
Place the cartridge into the inhaler. Be sure that the cartridge lies flat in the inhaler.

If any of these occur, throw away the cartridge
and load a new cartridge.

Close Inhaler
Lower the mouthpiece to close the inhaler (this will open the drug cartridge).
You should feel a snap when the inhaler is closed.

Step 3: Inhaling AFREZZA

Remove the Mouthpiece Cover
Important:Keep the inhaler level during and after removal of the purple mouthpiece cover.

Exhale
Hold the inhaler away from your mouth and fully blow out (exhale).

Position Inhaler in Mouth
Keeping your head level, place the mouthpiece in your mouth and tilt the inhaler down towards your chin, as shown.
Close your lips around the mouthpiece to form a seal.
Tilt the inhaler downward while keeping your head level.

Inhale Deeply and Hold Breath
With your mouth closed around the mouthpiece, inhale deeply through the inhaler.
Hold your breathfor as long as comfortable and at the same time remove the inhaler from your mouth. After holding your breath, exhale and continue to breathe normally.

Step 4: Removing a used cartridge

Replace Mouthpiece Cover
Place the purple mouthpiece cover back onto the inhaler.

Open Inhaler
Open the inhaler by lifting up the white mouthpiece.

Remove Cartridge
Remove the cartridge from the purple base.

Throw away (or recycle) the Cartridge
Throw away the used cartridge in your regular household trash.
Alternatively, the used cartridge (composed of HDPE, assigned recycling number 2) can be recycled.

Multiple cartridge dosing

If you need more than one (1) AFREZZA cartridge for your dose, see the AFREZZA dosage chart above (Figure B).

Repeat steps 2 through 4 for each AFREZZA cartridge you need for your prescribed AFREZZA dose.

How should I store AFREZZA?

Caring for your AFREZZA Inhaler:

Manufactured by: MannKind Corporation
Danbury, CT 06810
US License No. #2190
© 2016 – 2024 MannKind Corporation

This Instructions for Use has been approved by the U.S. Food and Drug Administration.
Revised: 01/2026

AFREZZA is a registered trademark of MannKind Corporation
Patent: www.mannkindcorp.com/patent-notices

PACKAGE LABEL

Principal Display Panel 90 − 4 unit cartridges and 2 inhalers

NDC 47918-874-90

Rx ONLY

afrezza®

(insulin human)
Inhalation Powder

4 units per
cartridge

90 single-use cartridges

FOR ORAL INHALATION ONLY

Carton Contains:

90 – 4 unit cartridges + 2 inhalers

Dispense the enclosed Medication Guide
to each patient

mannkind®

PACKAGE LABEL

Principal Display Panel 90 – 8 unit cartridges and 2 inhalers

NDC 47918-878-90

Rx ONLY

afrezza®

(insulin human)
Inhalation Powder

8 units per
cartridge

90 single-use cartridges

FOR ORAL INHALATION ONLY

Carton Contains:

90 – 8 unit cartridges + 2 inhalers

Dispense the enclosed Medication Guide
to each patient

mannkind®

PACKAGE LABEL

Principal Display Panel 90 – 12 unit cartridges and 2 inhalers

NDC 47918-891-90

Rx ONLY

afrezza®

(insulin human)
Inhalation Powder

12 units per
cartridge

90 single-use cartridges

FOR ORAL INHALATION ONLY

Carton Contains:

90 – 12 unit cartridges + 2 inhalers

Dispense the enclosed Medication Guide
to each patient

mannkind®

PACKAGE LABEL

Principal Display Panel 180 cartridges; 60 – 4 unit cartridges, 60 – 8 unit cartridges and 60 – 12 unit cartridges and 2 inhalers (Titration Pack)

NDC 47918-902-18

Rx ONLY

afrezza®

(insulin human)
Inhalation Powder

4 units per
cartridge

8 units per
cartridge

12 units per
cartridge

180 single-use cartridges

FOR ORAL INHALATION ONLY

Carton Contains:

60 – 4 unit cartridges

60 – 8 unit cartridges

60 – 12 unit cartridges

2 - inhalers

Dispense the enclosed
Medication Guide
to each patient

mannkind®

PACKAGE LABEL

Principal Display Panel 180 cartridges; 90 – 4 unit cartridges and 90 – 8 unit cartridges and 2 inhalers (Titration Pack)

NDC 47918-880-18

Rx ONLY

afrezza®

(insulin human)
Inhalation Powder

4 units per
cartridge

8 units per
cartridge

titration pack

180 single-use cartridges

FOR ORAL INHALATION ONLY

Carton Contains:

90 – 4 unit cartridges

90 – 8 unit cartridges

2 - inhalers

Dispense the enclosed
Medication Guide
to each patient

mannkind®

PACKAGE LABEL

Principal Display Panel 180 cartridges; 90 – 8 unit cartridges and 90 – 12 unit cartridges and 2 inhalers

NDC 47918-898-18

Rx ONLY

afrezza®

(insulin human)
Inhalation Powder

8 units per
cartridge

12 units per
cartridge

180 single-use cartridges

FOR ORAL INHALATION ONLY

Carton Contains:

90 – 8 unit cartridges

90 – 12 unit cartridges

2 - inhalers

Dispense the enclosed
Medication Guide
to each patient

mannkind®

PACKAGE LABEL

Principal Display Panel 30 cartridges;15 – 4 unit cartridges and 15 – 8 unit cartridges (Sample Kit)

NDC 47918-904-30

Rx ONLY

afrezza®

(insulin human)
Inhalation Powder

4 units per
cartridge

8 units per
cartridge

30 single-use cartridges

FOR ORAL INHALATION ONLY

Carton Contains:

15 – 4 unit cartridges

15 – 8 unit cartridges

1 - inhaler

Dispense the enclosed
Medication Guide
to each patient

mannkind®